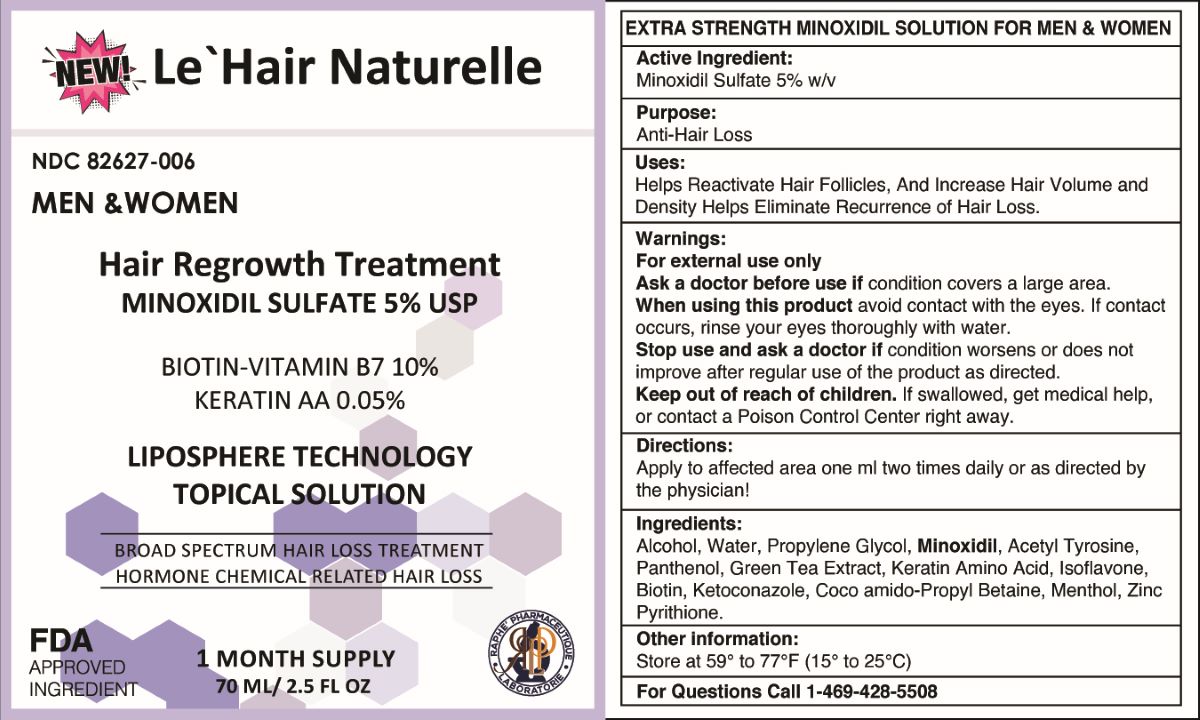 DRUG LABEL: Raphe Pharmaceutique
NDC: 82627-006 | Form: LIQUID
Manufacturer: AmWiner & Raphe Holdings LLC
Category: otc | Type: HUMAN OTC DRUG LABEL
Date: 20230902

ACTIVE INGREDIENTS: MINOXIDIL 50 mg/50 mg

PACKAGE LABEL

EXTRA STRENGTH MINOXIDIL SOLUTION FOR MEN & WOMEN

Active Ingredient: Minoxidil Sulfate 5% w/v

Purpose: Anti-Hair Loss

Uses: Helps Reactivate Hair Follicles, and Increase Hair Volume and Density

Helps Eliminate Recurrence of Hair Loss.

Warnings:

For external use only

Ask a doctor before use if condition covers a large area.

When using this product avoid contact with the eyes. If contact occurs, rinse your eyes thoroughly with water.

Stop use and ask a doctor if condition worsens or does not improve after regular use of the product as directed.

Keep out of reach of children. If swallowed, get medical help, or contact a Poison Control Center right away.

Directions

Apply to affected area one ml two times daily or as directed by the physician!

Ingredients: Alcohol, Water, Propylene Glycol, Minoxidil, Acetyl Tyrosine, Panthenol, Green Tea Extract, Keratin Amino Acid, Isoflavone, Biotin, Ketoconazole, Coco amido-Propyl Betaine, Menthol, Zinc Pyrithione.

Other information: Store at 59° to 77°F (15° to 25°C)

For Questions Call 1-469-428-5508